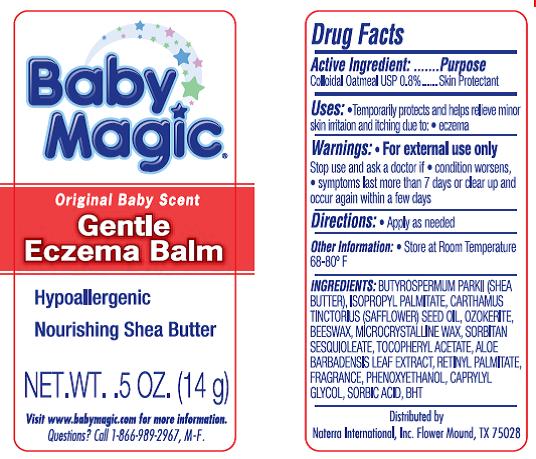 DRUG LABEL: Gentle Eczema Balm
NDC: 45765-5142 | Form: STICK
Manufacturer: Naterra  International INC.
Category: otc | Type: HUMAN OTC DRUG LABEL
Date: 20111012

ACTIVE INGREDIENTS: Oatmeal 0.112 g/14 g
INACTIVE INGREDIENTS: SHEA BUTTER; ISOPROPYL PALMITATE; SAFFLOWER OIL; CERESIN; MICROCRYSTALLINE WAX

Active Ingredient: Colloid Oatmeal USP (0.8%)

Purpose : Skin Protectant

Warnings: For external use only

Stop use and ask doctor if * condition worsens, * symptoms last more than 7 days or clear up and occur again within a few days.

Uses :
* Temporary protects and helps relieve minor skin irritation and itching due to * eczema

DOSAGE AND ADMINISTRATION

Direction ; Apply as needed

INACTIVE INGREDIENT

Fragrance